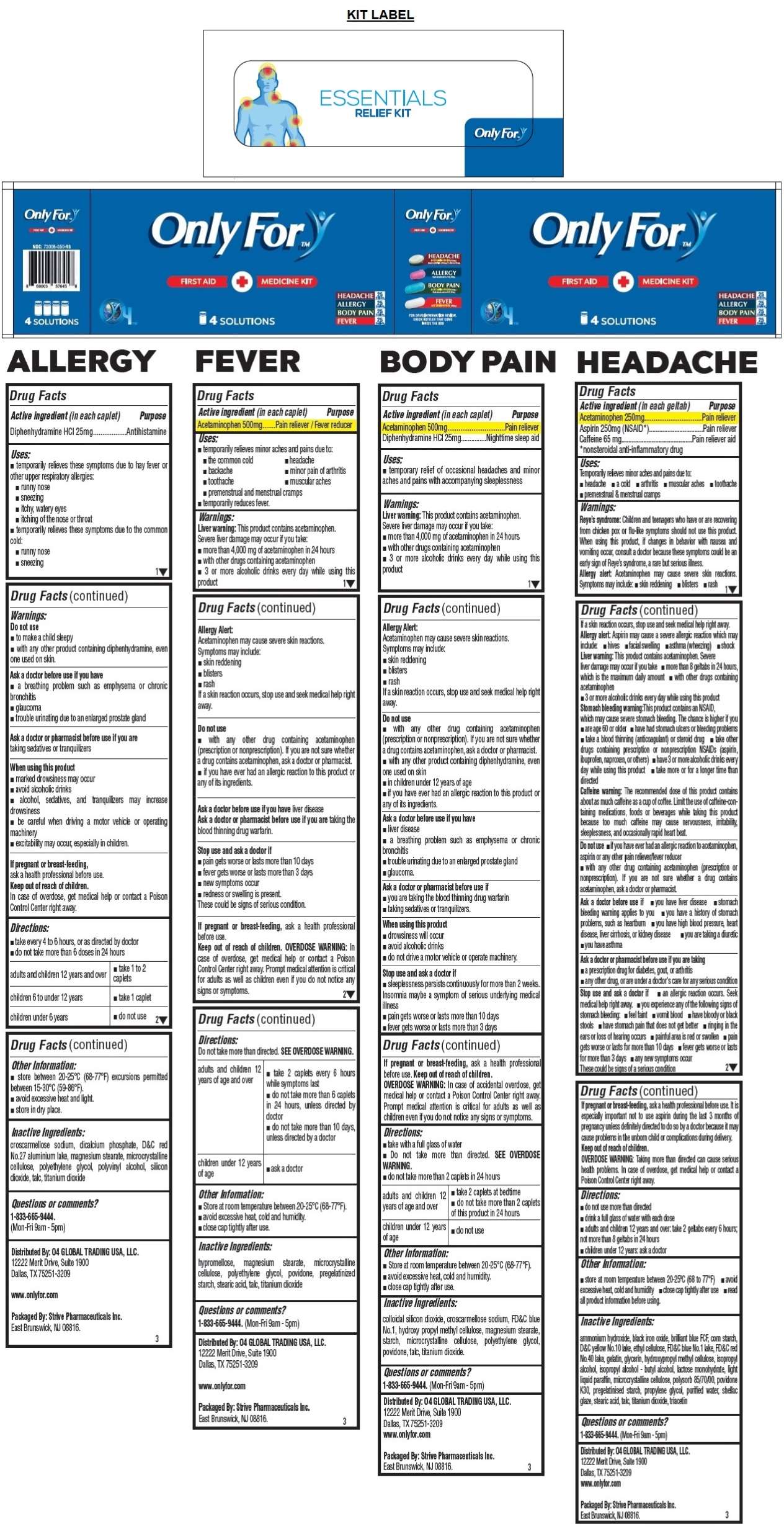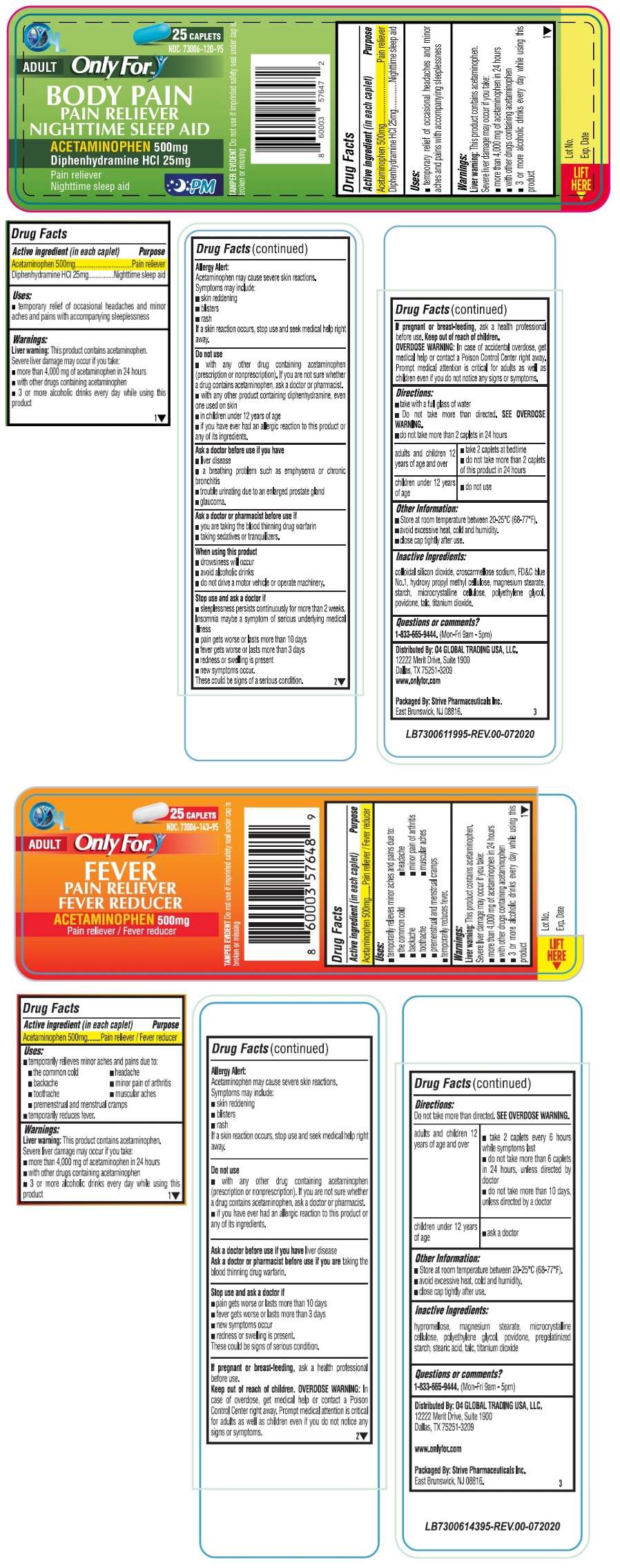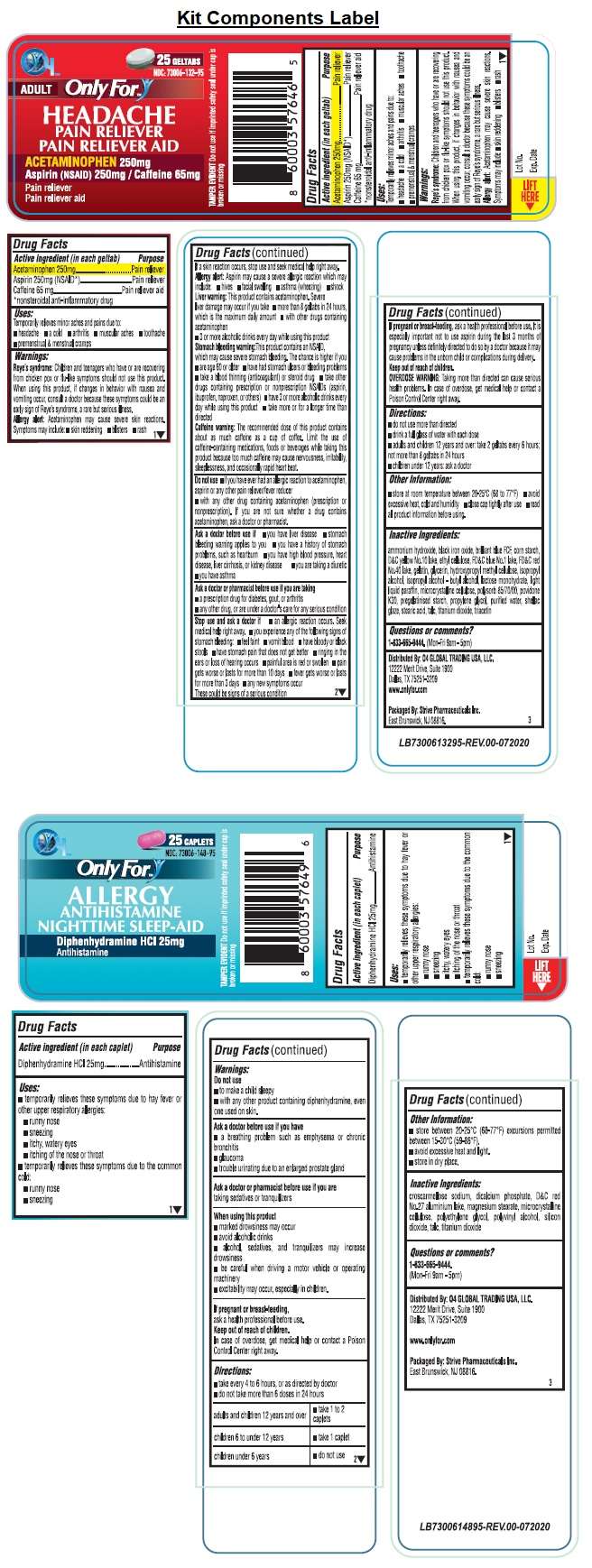 DRUG LABEL: Only For FIRST AID MEDICINE
NDC: 73006-350 | Form: KIT | Route: ORAL
Manufacturer: O4 Global Trading Usa, Llc
Category: otc | Type: HUMAN OTC DRUG LABEL
Date: 20201223

ACTIVE INGREDIENTS: ACETAMINOPHEN 250 mg/1 1; ASPIRIN 250 mg/1 1; CAFFEINE 65 mg/1 1; DIPHENHYDRAMINE HYDROCHLORIDE 25 mg/1 1; ACETAMINOPHEN 500 mg/1 1; DIPHENHYDRAMINE HYDROCHLORIDE 25 mg/1 1; ACETAMINOPHEN 500 mg/1 1
INACTIVE INGREDIENTS: AMMONIA; FERROSOFERRIC OXIDE; FD&C BLUE NO. 1; STARCH, CORN; D&C YELLOW NO. 10; ETHYLCELLULOSE, UNSPECIFIED; FD&C RED NO. 40; GELATIN; GLYCERIN; HYPROMELLOSES; ISOPROPYL ALCOHOL; BUTYL ALCOHOL; LACTOSE MONOHYDRATE; LIGHT MINERAL OIL; MICROCRYSTALLINE CELLULOSE; SORBITOL SOLUTION; POVIDONE, UNSPECIFIED; PROPYLENE GLYCOL; WATER; SHELLAC; STEARIC ACID; TALC; TITANIUM DIOXIDE; TRIACETIN; CROSCARMELLOSE SODIUM; ANHYDROUS DIBASIC CALCIUM PHOSPHATE; D&C RED NO. 27 ALUMINUM LAKE; MAGNESIUM STEARATE; MICROCRYSTALLINE CELLULOSE; POLYETHYLENE GLYCOL, UNSPECIFIED; POLYVINYL ALCOHOL, UNSPECIFIED; SILICON DIOXIDE; TALC; TITANIUM DIOXIDE; SILICON DIOXIDE; CROSCARMELLOSE SODIUM; FD&C BLUE NO. 1; HYPROMELLOSE, UNSPECIFIED; MAGNESIUM STEARATE; STARCH, CORN; MICROCRYSTALLINE CELLULOSE; POLYETHYLENE GLYCOL 400; POVIDONE, UNSPECIFIED; TALC; TITANIUM DIOXIDE; HYPROMELLOSE, UNSPECIFIED; MAGNESIUM STEARATE; MICROCRYSTALLINE CELLULOSE; POLYETHYLENE GLYCOL, UNSPECIFIED; POVIDONE, UNSPECIFIED; STARCH, CORN; STEARIC ACID; TALC; TITANIUM DIOXIDE

Only For™ FIRST AID + MEDICINE KIT

ONLY FOR HEADACHE- acetaminophen, aspirin, caffeine tablet

Drug Facts

Active ingredient (in each geltab)

Acetaminophen 250mg

Aspirin 250mg (NSAID*)

Caffeine 65 mg

*nonsteroidal anti-inflammatory drug

Purpose

Pain reliever

Pain reliever

Pain reliever aid

Uses:

Temporarily relieves minor aches and pains due to:

• headache • a cold • arthritis • muscular aches • toothache • premenstrual & menstrual cramps

Warnings:

Reye's syndrome: Children and teenagers who have or are recovering from chicken pox or flue-like symptoms should not use this product. When using this product, if changes in behavior with nausea and vomiting occur, consult a doctor because these symptoms could be an early sign of Reye's syndrome, a rare but serious illness.

Allergy alert: Acetaminophen may cause severe skin reactions. Symptoms may include: • skin reddening • blisters • rash

If a skin reaction occurs, stop use and seek medical help right away.

Allergy alert: Aspirin may cause a severe allergic reaction which may include: • hives • facial swelling • asthma (wheezing) • shock

Liver warning: This product contains acetaminophen. Severe liver damage may occur if you take • more than 8 geltabs in 24 hours, which is the maximum daily amount • with other drugs containing acetaminophen • 3 or more alcoholic drinks every day while using this product

Stomach bleeding warning: This product contains an NSAID, which may cause severe stomach bleeding. The chance is higher if you • are age 60 or older • have had stomach ulcers or bleeding problems • take a blood thinning (anticoagulant) or steroid drug • take other drugs containing prescription or nonprescription NSAIDs (aspirin, ibuprofen, or others) • have 3 or more alcoholic drinks every day while using this product • take more or for a longer time than directed

Caffeine warning: The recommended dose of this product contains about a much caffeine as cup of coffee. Limit the use of caffeine-containing medications, foods or beverages while taking this product because too much caffeine may cause nervousness, irritability, sleeplessness, and occasionally rapid heart beat.

Do not use • if you have ever had an allergic reaction to acetaminophen, aspirin or any other pain reliever/fever reducer • with any other drug containing acetaminophen (prescription or nonprescription). If you are not sure whether a drug contains acetaminophen, ask a doctor or pharmacist.

Ask a doctor before use if • you have liver disease • stomach bleeding warning applies to you • you have a history of stomach problems, such as heartburn • you have high blood pressure, heart disease, liver cirrhosis, or kidney disease • you are taking a diuretic • you have asthma

Ask a doctor or pharmacist before use if you are taking

• a prescription drug for diabetes, gout, or arthritis

• any other drug, or are under a doctor's care for any serious condition

Stop use and ask a doctor if • an allergic reaction occurs. Seek medical help right away. • you experience any of the following signs of stomach bleeding: • feel faint • vomit blood • have bloody or black stools • have stomach pain that does not get better • ringing in the ears or loss of hearing occurs • painful area is red or swollen • pain gets worse or lasts for more than 10 days • fever gets worse or lasts for more than 3 days • any new symptoms occur

These could be signs of a serious condition

If pregnant or breast-feeding, ask a health professional before use. It is especially important not to use aspirin during the last 3 months of pregnancy unless definitely directed to do so by a doctor because it may cause problems in the unborn child or compliments during delivery.

Keep out of reach of children.

OVERDOSE WARNING: Taking more than directed can cause serious health problems. In case overdose. get medical help or contact a Poison Control Center right away.

Directions:

• do not use more than directed

• drink a full glass of water with each dose

• adults and children 12 years and over: take 2 geltabs every 6 hours; not more than 8 geltabs in 24 hours

• children under 12 years: ask a doctor

Other Information:

• store at room temperature between 20-25°C (68 to 77°F) • avoid excessive heat, cold and humidity • close cap tightly after use • read all product information before using.

Inactive Ingredients:

ammonium hydroxide, black iron oxide, brilliant blue FCF, corn starch, D&C yellow No.10 lake, ethyl cellulose, FD&C blue No.1 lake, FD&C red No.40 lake, gelatin, glycerin, hydroxypropyl methyl cellulose, isopropyl alcohol, isopropyl alcohol - butyl alcohol, lactose monohydrate, light liquid paraffin, microcrystalline cellulose, polysorb 85/70/00, povidone K30, pregelatinised starch, propylene glycol, purified water, shellac glaze, stearic acid, talc, titanium dioxide, triacetin

Questions or comments?

1-833-665-9444. (Mon-Fri 9am-5pm)

ONLY FOR ALLERGY- diphenhydramine hcl tablet

Drug Facts

Active ingredient (in each caplet)

Diphenhydramine HCl 25mg

Purpose

Antihistamine

Uses:

• temporarily relieves these symptoms due to hay fever or other upper respiratory allergies:
• runny nose
• sneezing
• itchy, watery eyes
• itching of the nose or throat

• temporarily relieves these symptoms due to the common cold:
• runny nose
• sneezing

Warnings:

Do not use
• to make a child sleepy
• with any other product containing diphenhydramine, even one used on skin.

Ask a doctor before use if you have
• a breathing problem such as emphysema or chronic bronchitis
• glaucoma
• trouble urinating due to an enlarged prostate gland

Ask a doctor or pharmacist before use if you are

taking sedatives or tranquilizers

When using this product
• marked drowsiness may occur
• avoid alcoholic drinks
• alcohol, sedatives, and tranquilizers may increase drowsiness
• be careful when driving a motor vehicle or operating machinery
• excitability may occur, especially in children.

If pregnant or breast-feeding,
ask a health professional before use.

Keep out of reach of children.
In case of overdose, get medical help or contact a Poison Control Center right away.

Directions:

• take every 4 to 6 hours, or as directed by doctor

• do not take more than 6 doses in 24 hours

adults and children 12 years and over | • take 1 to 2 caplets
children 6 to under 12 years | • take 1 caplet

Other Information:

• store between 20-25°C (68-77°F) excursions permitted between 15-30°C (59-86°F).
• avoid excessive heat and light.
• store in dry place.

Inactive Ingredients:

croscarmellose sodium, dicalcium phosphate, D&C red No.27 aluminium lake, magnesium stearate, microcrystalline cellulose, polyethylene glycol, polyvinyl alcohol, silicon dioxide, talc, titanium dioxide

Questions or comments?

1-833-665-9444.
(Mon-Fri 9am - 5pm)

ONLY FOR BODY PAIN- acetaminophen, diphenhydramine hcl tablet

Drug Facts

Active ingredient (in each caplet)

Acetaminophen 500mg

Diphenhydramine HCl 25mg

Purpose

Pain reliever

Nighttime sleep aid

Uses:

• temporary relief of occasional headaches and minor aches and pains with accompanying sleeplessness

Warnings:

Liver warning: This product contains acetaminophen. Severe liver damage may occur if you take:

• more than 4,000 mg of acetaminophen in 24 hours

• with other drugs containing acetaminophen

• 3 or more alcoholic drinks every day while using this product

Allergy Alert:

Acetaminophen may cause severe skin reactions.

Symptoms may include:

• skin reddening

• blisters

• rash

If a skin reaction occurs, stop use and seek medical help right away.

Do not use

• with any other drug containing acetaminophen (prescription or nonprescription). If you are not sure whether a drug contains acetaminophen, ask a doctor or pharmacist.

• with any other product containing diphenhydramine, even one used on skin

• in children under 12 years of age

• if you have ever had any allergic reaction to this product or any of its ingredients.

Ask a doctor before use if you have

• liver disease

• a breathing problem such as emphysema or chronic bronchitis

• trouble urinating due to an enlarged prostate gland

• glaucoma.

Ask a doctor or pharmacist before use if

• you are taking the blood thinning drug warfarin

• taking sedatives or tranquilizers.

When using this product

• drowsiness will occur

• avoid alcoholic drinks

• do not drive a motor vehicle or operate machinery.

Stop use and ask a doctor if

• sleeplessness persists continuously for more than 2 weeks. Insomnia may be a symptom of serious underlying medical illness.

• pain gets worse or lasts more than 10 days

• fever gets worse or last more than 3 days

If pregnant or breast-feeding, ask a health professional before use.

Keep out of reach of children.

OVERDOSE WARNINGS: In case of accidental overdose, get medical help or contact a Poison Control Center right away. Prompt medical attention is critical for adults as well as for children even if you do not notice any signs or symptoms.

Directions:

• take with a full glass of water

• Do not take more than directed. SEE OVERDOSE WARNING.

• do not take more than 2 caplets in 24 hours

adults and children 12 years of age and over | • take 2 caplets at bedtime; • do not take more than 2 caplets of this product in 24 hours
children under 12 years of age | • do not use

Other Information:

• Store at room temperature between 20-25°C (68-77°F).

• avoid excessive heat, cold and humidity.

• close cap tightly after use.

Inactive Ingredients:

colloidal silicon dioxide, croscarmellose sodium, FD&C blue No.1, hydroxy propyl methyl cellulose, magnesium stearate, starch, microcrystalline cellulose, polyethylene glycol, povidone, talc, titanium dioxide.

Questions or comments?

1-833-665-9444. (Mon-Fri 9am-5pm)

ONLY FOR FEVER- acetaminophen tablet

Drug Facts

Active ingredient (in each caplet)

Acetaminophen 500mg

Purpose

Pain reliever / Fever reducer

Uses:

• temporary relief minor aches and pains due to:

• the common cold

• backache

• toothache

• premenstrual and menstrual cramps

• temporarily reduces fever.

• headache

• minor pain of arthritis

• muscular aches

• premenstrual and menstrual cramps

• temporarily reduces fever.

Warnings:

Liver warning: This product contains acetaminophen. Severe liver damage may occur if you take:

• more than 4,000 mg of acetaminophen in 24 hours

• with other drugs containing acetaminophen

• 3 or more alcoholic drinks every day while using this product

Allergy Alert:

Acetaminophen may cause severe skin reactions.

Symptoms may include:

• skin reddening

• blisters

• rash

If a skin reaction occurs, stop use and seek medical help right away.

Do not use

• with any other drug containing acetaminophen (prescription or nonprescription). If you are not sure whether a drug contains acetaminophen, ask a doctor or pharmacist.

• if you have ever had any allergic reaction to this product or any of its ingredients.

Ask a doctor before use if you have liver disease

Ask a doctor or pharmacist before use if are taking the blood thinning drug warfarin

Stop use and ask a doctor if

• pain gets worse or lasts more than 10 days

• fever gets worse or last more than 3 days

• new symptoms occur.

• redness or swelling is present

These could be signs of a serious condition.

If pregnant or breast-feeding, ask a health professional before use.

Keep out of reach of children. OVERDOSE WARNINGS: In case of accidental overdose, get medical help or contact a Poison Control Center right away. Prompt medical attention is critical for adults as well as for children even if you do not notice any signs or symptoms.

Directions:

Do not take more than directed. SEE OVERDOSE WARNING.

adults and children 12 years of age and over | • take 2 caplets every 6 hours while symptoms last; • do not take more than 6 caplets in 24 hours, unless directed by doctor; • do not take more than 10 days, unless directed by a doctor
children under 12 years of age | • ask a doctor

Other Information:

• Store at room temperature between 20-25°C (68-77°F).

• avoid excessive heat, cold and humidity.

• close cap tightly after use.

Inactive Ingredients:

hypromellose, magnesium stearate, microcrystalline cellulose, polyethylene glycol, povidone, pregelatinized starch, stearic acid, talc, titanium dioxide

Questions or comments?

1-833-665-9444. (Mon-Fri 9am-5pm)

Only For™ FIRST AID + MEDICINE KIT

4 SOLUTIONS

HEADACHE 25 Geltabs

ACETAMINOPHEN 250mg / Aspirin (NSAID) 250mg / Caffeine 65mg

ALLERGY 25 Caplets

Diphenhydramine HCl 25mg

BODY PAIN 25 Caplets

ACETAMINOPHEN 500mg / Diphenhydramine HCl 25mg

FEVER 25 Caplets

ACETAMINOPHEN 500mg

FOR DRUG INFORMATION REVIEW, CHECK BOTTLES THAT COME INSIDE THE BOX
Distributed By: O4 GLOBAL TRADING USA, LLC.

12222 Merit Drive, Suite 1900

Dallas, TX 75251-3209

www.onlyfor.com

Packaged By: Strive Pharmaceuticals Inc.

East Brunswick, NJ 08816.